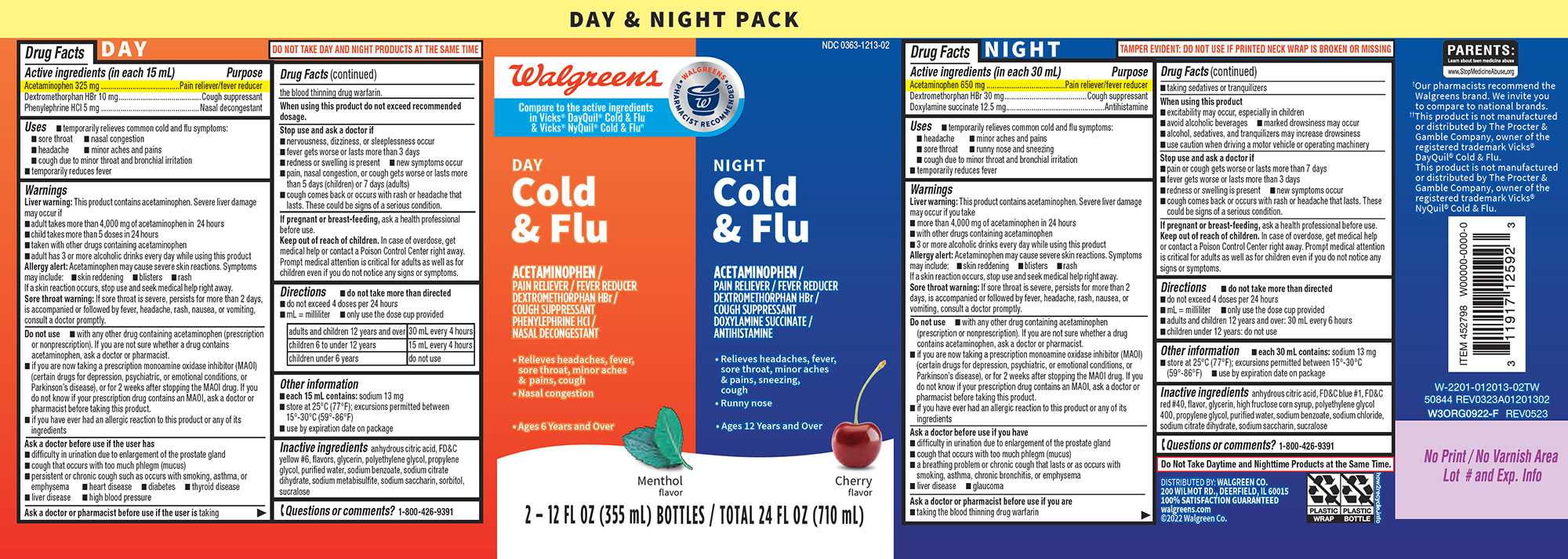 DRUG LABEL: Cold and Flu
NDC: 0363-1213 | Form: KIT | Route: ORAL
Manufacturer: Walgreen Company
Category: otc | Type: HUMAN OTC DRUG LABEL
Date: 20251115

ACTIVE INGREDIENTS: ACETAMINOPHEN 325 mg/15 mL; DEXTROMETHORPHAN HYDROBROMIDE 10 mg/15 mL; PHENYLEPHRINE HYDROCHLORIDE 5 mg/15 mL; ACETAMINOPHEN 650 mg/30 mL; DEXTROMETHORPHAN HYDROBROMIDE 30 mg/30 mL; DOXYLAMINE SUCCINATE 12.5 mg/30 mL
INACTIVE INGREDIENTS: ANHYDROUS CITRIC ACID; FD&C YELLOW NO. 6; GLYCERIN; POLYETHYLENE GLYCOL, UNSPECIFIED; PROPYLENE GLYCOL; WATER; SODIUM BENZOATE; TRISODIUM CITRATE DIHYDRATE; SODIUM METABISULFITE; SACCHARIN SODIUM; SORBITOL; SUCRALOSE; ANHYDROUS CITRIC ACID; FD&C BLUE NO. 1; FD&C RED NO. 40; GLYCERIN; HIGH FRUCTOSE CORN SYRUP; POLYETHYLENE GLYCOL 400; PROPYLENE GLYCOL; WATER; SODIUM BENZOATE; SODIUM CHLORIDE; TRISODIUM CITRATE DIHYDRATE; SACCHARIN SODIUM; SUCRALOSE

Walgreens 44-012013 Wrap Delisted

Active ingredients (in each 15 mL) (Day)

Acetaminophen 325 mg
Dextromethorphan HBr 10 mg
Phenylephrine HCl 5 mg

Purpose

Pain reliever/fever reducer
Cough suppressant
Nasal decongestant

Uses

- temporarily relieves common cold and flu symptoms:
  - sore throat
  - nasal congestion
  - minor aches and pains
  - cough due to minor throat and bronchial irritation
  - headache
- temporarily reduces fever

Warnings

Liver warning: This product contains acetaminophen. Severe liver damage may occur if

- adult takes more than 4,000 mg of acetaminophen in 24 hours
- child takes more than 5 doses in 24 hours
- taken with other drugs containing acetaminophen
- adult has 3 or more alcoholic drinks every day while using this product

Allergy alert: Acetaminophen may cause severe skin reactions. Symptoms may include:

- skin reddening
- blisters
- rash

If a skin reaction occurs, stop use and seek medical help right away.

Sore throat warning: If sore throat is severe, persists for more than 2 days, is accompanied or followed by fever, headache, rash, nausea, or vomiting, consult a doctor promptly.

Do not use

- with any other drug containing acetaminophen (prescription or nonprescription). If you are not sure whether a drug contains acetaminophen, ask a doctor or pharmacist.
- if you are now taking a prescription monoamine oxidase inhibitor (MAOI) (certain drugs for depression, psychiatric, or emotional conditions, or Parkinson’s disease), or for 2 weeks after stopping the MAOI drug. If you do not know if your prescription drug contains an MAOI, ask a doctor or pharmacist before taking this product.
- if you have ever had an allergic reaction to this product or any of its ingredients

Ask a doctor before use if the user has

- high blood pressure
- difficulty in urination due to enlargement of the prostate gland
- cough that occurs with too much phlegm (mucus)
- liver disease
- persistent or chronic cough such as occurs with smoking, asthma, or emphysema
- heart disease
- diabetes
- thyroid disease

Ask a doctor or pharmacist before use if the user is

taking the blood thinning drug warfarin.

When using this product

do not exceed recommended dosage.

Stop use and ask a doctor if

- nervousness, dizziness, or sleeplessness occur
- fever gets worse or lasts more than 3 days
- redness or swelling is present
- new symptoms occur
- pain, nasal congestion, or cough gets worse or lasts more than 5 days (children) or 7 days (adults)
- cough comes back or occurs with rash or headache that lasts. These could be signs of a serious condition.

If pregnant or breast-feeding,

ask a health professional before use.

Keep out of reach of children.

In case of overdose, get medical help or contact a Poison Control Center right away. Prompt medical attention is critical for adults as well as for children even if you do not notice any signs or symptoms.

Directions

- do not take more than directed
- do not exceed 4 doses per 24 hours
- mL = milliliter
- only use the dose cup provided

adults and children 12 years and over | 30 mL every 4 hours
children 6 to under 12 years | 15 mL every 4 hours
children under 6 years | do not use

Other information

- each 15 mL contains: sodium 13 mg
- store at 25°C (77°F); excursions permitted between 15°-30°C (59°-86°F)
- use by expiration date on package

Inactive ingredients

anhydrous citric acid, FD&C yellow #6, flavors, glycerin, polyethylene glycol, propylene glycol, purified water, sodium benzoate, sodium citrate dihydrate, sodium metabisulfite, sodium saccharin, sorbitol, sucralose

Questions or comments?

1-800-426-9391

Active ingredients (in each 30 mL) (Night)

Acetaminophen 650 mg
Dextromethorphan HBr 30 mg
Doxylamine succinate 12.5 mg

Purpose

Pain reliever/fever reducer
Cough suppressant
Antihistamine

Uses

- temporarily relieves common cold and flu symptoms:
  - headache
  - minor aches and pains
  - sore throat
  - runny nose and sneezing
  - cough due to minor throat and bronchial irritation
- temporarily reduces fever

Warnings

Liver warning: This product contains acetaminophen. Severe liver damage may occur if you take

- more than 4,000 mg of acetaminophen in 24 hours
- with other drugs containing acetaminophen
- 3 or more alcoholic drinks every day while using this product

Allergy alert: Acetaminophen may cause severe skin reactions. Symptoms may include:

- skin reddening
- blisters
- rash

If a skin reaction occurs, stop use and seek medical help right away.

Sore throat warning: If sore throat is severe, persists for more than 2 days, is accompanied or followed by fever, headache, rash, nausea, or vomiting, consult a doctor promptly.

Do not use

- with any other drug containing acetaminophen (prescription or nonprescription). If you are not sure whether a drug contains acetaminophen, ask a doctor or pharmacist.
- if you are now taking a prescription monoamine oxidase inhibitor (MAOI) (certain drugs for depression, psychiatric, or emotional conditions, or Parkinson’s disease), or for 2 weeks after stopping the MAOI drug. If you do not know if your prescription drug contains an MAOI, ask a doctor or pharmacist before taking this product.
- if you have ever had an allergic reaction to this product or any of its ingredients

Ask a doctor before use if you have

- liver disease
- glaucoma
- difficulty in urination due to enlargement of the prostate gland
- cough that occurs with too much phlegm (mucus)
- a breathing problem or chronic cough that lasts or as occurs with smoking, asthma, chronic bronchitis, or emphysema

Ask a doctor or pharmacist before use if you are

- taking the blood thinning drug warfarin
- taking sedatives or tranquilizers

When using this product

- excitability may occur, especially in children
- avoid alcoholic beverages
- marked drowsiness may occur
- alcohol, sedatives, and tranquilizers may increase drowsiness
- use caution when driving a motor vehicle or operating machinery

Stop use and ask a doctor if

- pain or cough gets worse or lasts more than 7 days
- fever gets worse or lasts more than 3 days
- redness or swelling is present
- new symptoms occur
- cough comes back or occurs with rash or headache that lasts. These could be signs of a serious condition.

If pregnant or breast-feeding,

ask a health professional before use.

Keep out of reach of children.

In case of overdose, get medical help or contact a Poison Control Center right away. Prompt medical attention is critical for adults as well as for children even if you do not notice any signs or symptoms.

Directions

- do not take more than directed
- do not exceed 4 doses per 24 hours
- mL = milliliter
- only use the dose cup provided
- adults and children 12 years and over: 30 mL every 6 hours
- children under 12 years: do not use

Other information

- each 30 mL contains: sodium 13 mg
- store at 25°C (77°F); excursions permitted between 15°-30°C (59°-86°F)
- use by expiration date on package

Inactive ingredients

anhydrous citric acid, FD&C blue #1, FD&C red #40, flavor, glycerin, high fructose corn syrup, polyethylene glycol 400, propylene glycol, purified water, sodium benzoate, sodium chloride, sodium citrate dihydrate, sodium saccharin, sucralose

Questions or comments?

1-800-426-9391

Principal display panel

DAY & NIGHT PACK

NDC 0363-1213-02

Walgreens

WALGREENS PHARMACIST RECOMMENDED†

Compare to the active ingredients
in Vicks® DayQuil® Cold & Flu
& Vicks® NyQuil® Cold & Flu††

DAY
Cold
& Flu

ACETAMINOPHEN /
PAIN RELIEVER / FEVER REDUCER
DEXTROMETHORPHAN HBr /
COUGH SUPPRESSANT
PHENYLEPHRINE HCl /
NASAL DECONGESTANT

• Relieves headaches, fever,
sore throat, minor aches
& pains, cough
• Nasal congestion

• Ages 6 Years and Over

Menthol
flavor

NIGHT
Cold
& Flu

ACETAMINOPHEN /
PAIN RELIEVER / FEVER REDUCER
DEXTROMETHORPHAN HBr /
COUGH SUPPRESSANT
DOXYLAMINE SUCCINATE /
ANTIHISTAMINE

Relieves headaches, fever,
sore throat, minor aches
& pains, sneezing,
cough
• Runny nose

• Ages 12 Years and Over

Cherry
flavor

2 – 12 FL OZ (355 mL) BOTTLES / TOTAL 24 FL OZ (710 mL)

DO NOT TAKE DAY AND NIGHT PRODUCTS AT THE SAME TIME

TAMPER EVIDENT: DO NOT USE IF PRINTED NECK WRAP IS BROKEN OR MISSING

PARENTS:
Learn about teen medicine abuse
www.StopMedicineAbuse.org

Do Not Take Daytime and Nighttime Products at the Same Time.

†Our pharmacists recommend the
Walgreens brand. We invite you
to compare to national brands.
††This product is not manufactured
or distributed by The Procter &
Gamble Company, owner of the
registered trademark Vicks®
DayQuil® Cold & Flu.
This product is not manufactured
or distributed by The Procter &
Gamble Company, owner of the
registered trademark Vicks®
NyQuil® Cold & Flu.

DISTRIBUTED BY: WALGREEN CO.
200 WILMOT RD., DEERFIELD, IL 60015
100% SATISFACTION GUARANTEED
walgreens.com
©2022 Walgreen Co.

W-2201-012013-02
50844 REV0323A01201302

Walgreens 44-012013